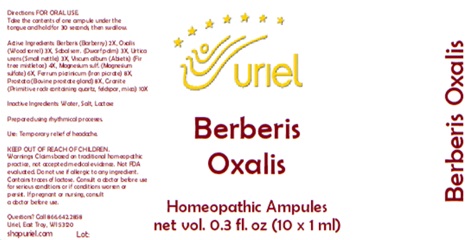 DRUG LABEL: Berberis Oxalis
NDC: 48951-2161 | Form: LIQUID
Manufacturer: Uriel Pharmacy Inc.
Category: homeopathic | Type: HUMAN OTC DRUG LABEL
Date: 20250528

ACTIVE INGREDIENTS: BERBERIS VULGARIS ROOT BARK 2 [hp_X]/1 mL; OXALIS STRICTA WHOLE 3 [hp_X]/1 mL; SAW PALMETTO 3 [hp_X]/1 mL; URTICA URENS 3 [hp_X]/1 mL; VISCUM ALBUM FRUITING TOP 4 [hp_X]/1 mL; MAGNESIUM SULFATE, UNSPECIFIED FORM 6 [hp_X]/1 mL; BOS TAURUS PROSTATE GLAND 8 [hp_X]/1 mL; PENOXSULAM 10 [hp_X]/1 mL; FERRIC PICRATE 8 [hp_X]/1 mL
INACTIVE INGREDIENTS: WATER; SODIUM CHLORIDE

Berberis Oxalis

INDICATIONS AND USAGE

Directions: FOR ORAL USE ONLY.

DOSAGE AND ADMINISTRATION

Take the contents of one ampule
under the tongue and hold for
30 seconds, then swallow.

ACTIVE INGREDIENT

Active Ingredients: Berberis (Barberry) 2X, Oxalis (Wood sorrel) 3X, Sabal serr. (Dwarf palm) 3X, Urtica urens (Small nettle) 3X, Viscum Abietis (Fir tree mistletoe) 4X, Magnesium sulf. (Magnesium sulfate) 6X, Prostata (Bovine prostate gland) 8X, Ferrum picrinicum (Iron picrate) 8X, Granite (Primitive rock containing quartz, feldspar, mica) 10X

Inactive Ingredients: Water, Salt, Lactose

Prepared using rhythmical processes.

PURPOSE

Use: Temporary relief of headache.

KEEP OUT OF REACH OF CHILDREN.

WARNINGS

Warnings: Claims based on traditional homeopathic practice, not accepted medical evidence. Not FDA evaluated. Do not use if allergic to any ingredient. Contains traces of lactose. Consult a doctor before use for serious conditions or if conditions worsen or
persist. If pregnant or nursing, consult a doctor before use.

Questions? Call 866.642.2858
Uriel, East Troy, WI 53120
shopuriel.com Lot: